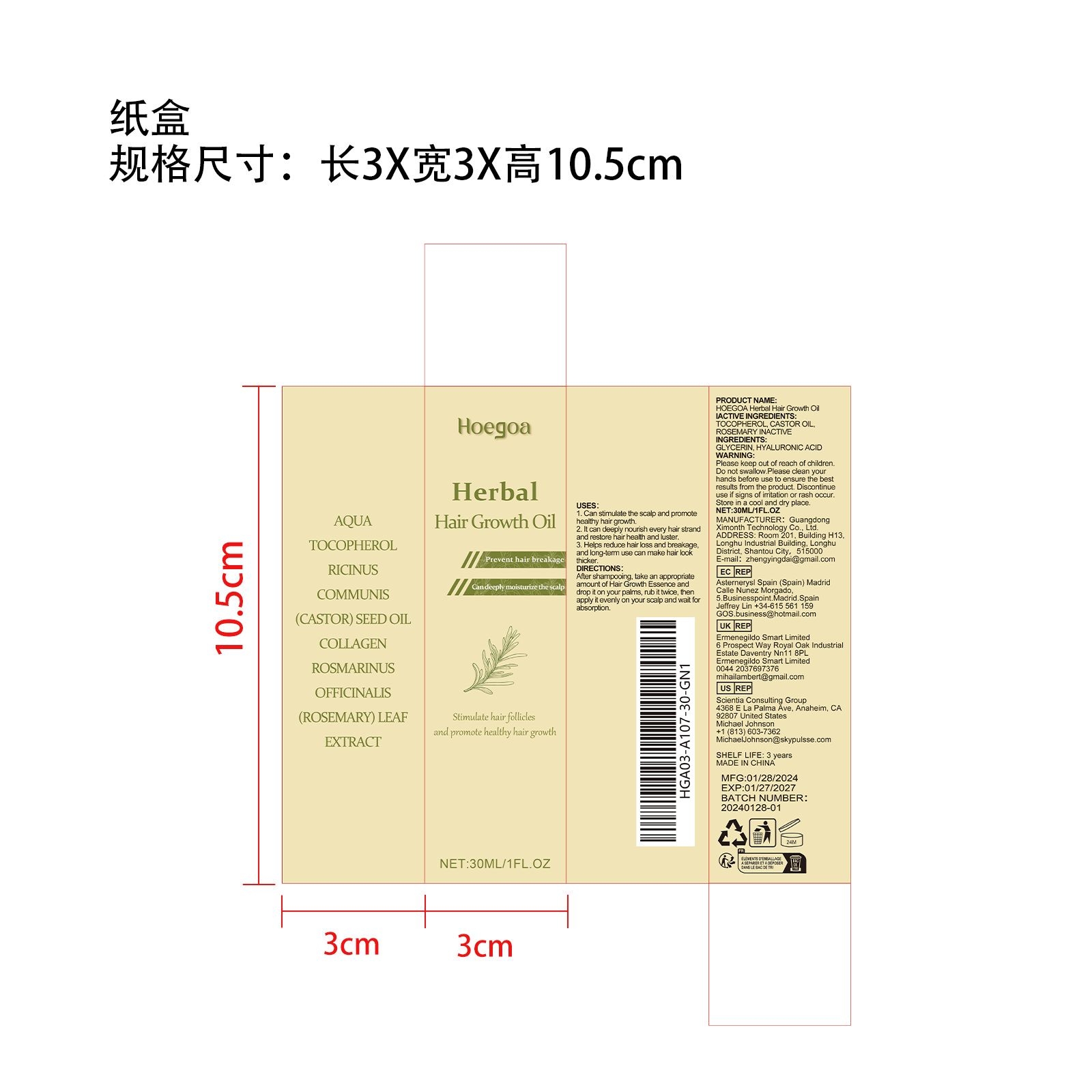 DRUG LABEL: HOEGOA Herbal Hair Growth OiI
NDC: 84660-058 | Form: LIQUID
Manufacturer: Guangdong Ximonth Technology Co., Ltd.
Category: otc | Type: HUMAN OTC DRUG LABEL
Date: 20241102

ACTIVE INGREDIENTS: CASTOR OIL 3 mg/30 mg; ROSEMARY 4.5 mg/30 mg; TOCOPHEROL 9 mg/30 mg
INACTIVE INGREDIENTS: GLYCERIN 4.5 mg/30 mg; HYALURONIC ACID 9 mg/30 mg

ACTIVE INGREDIENTS

TOCOPHEROL,CASTOR OIL,ROSEMARY

PURPOSE

1. Can stimulate the scalp and promote healthy hair growth.

2. It can deeply nourish every hair strand and restore hair health and luster.

3. Helps reduce hair loss and breakage, and long-term use can make hair look thicker.

USES

After shampooing, take an appropriate amount of Hair Growth Essence and drop it on your palms, rub it twice, then apply it evenly on your scalp and wait for absorption.

WARNINGS

Please keep out of reach of children.Do not swallow.Please clean your hands before use to ensure the best results from the product.Discontinue use if signs of irritation or rash occur.Store in a cool and dry place.

STOP USE

Discontinue use if signs of irritation or rash occur.

DO NOT USE

Discontinue use if signs of irritation or rash occur.

KEEP OUT OF REACH OF CHILDREN

Please keep out of reach of children.Do not swallow.

STORAGE AND HANDLING

Store in a cool and dry place.

INACTIVE INGREDIENT

GLYCERIN,HYALURONIC ACID